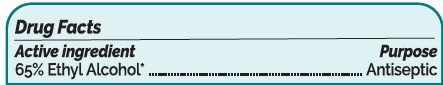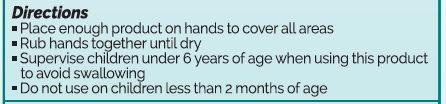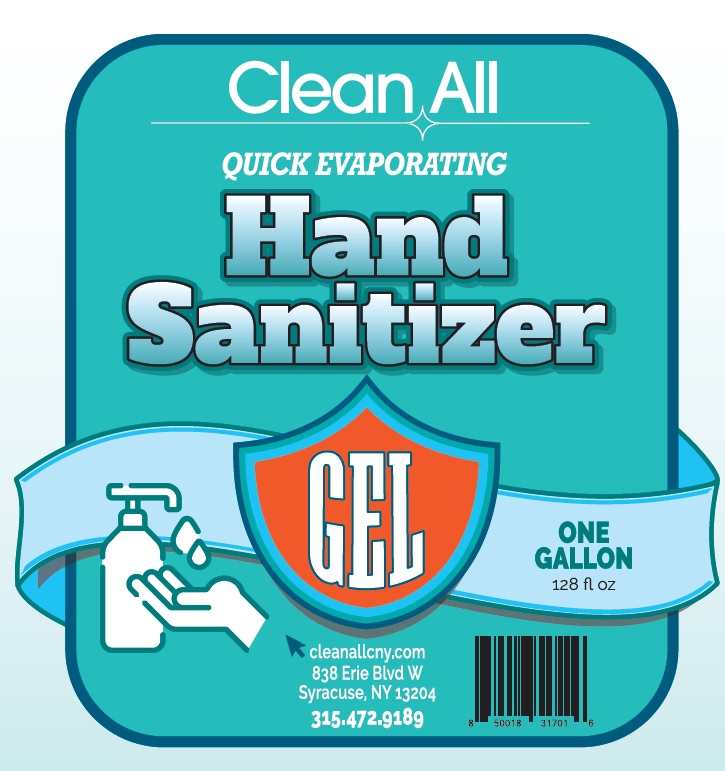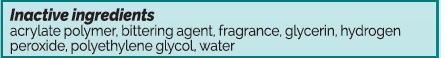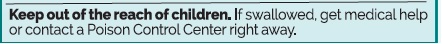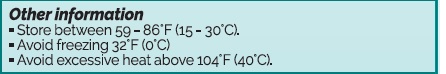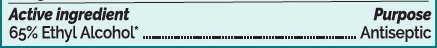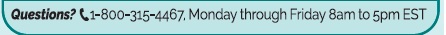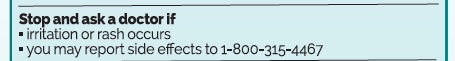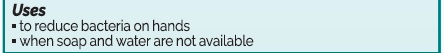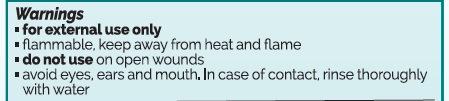 DRUG LABEL: Clean All Gel Hand Sanitizer
NDC: 75660-104 | Form: GEL
Manufacturer: Solvents and Petroleum Inc
Category: otc | Type: HUMAN OTC DRUG LABEL
Date: 20201013

ACTIVE INGREDIENTS: ALCOHOL 65 mL/100 mL
INACTIVE INGREDIENTS: POLYETHYLENE GLYCOL, UNSPECIFIED 2 mL/100 mL; GLYCERIN 1.35 mL/100 mL; HYDROGEN PEROXIDE 0.18 mL/100 mL; WATER 30.96 mL/100 mL; DENATONIUM BENZOATE 0.01 mL/100 mL; ACRYLATES/VINYL ISODECANOATE CROSSPOLYMER (10000 MPA.S NEUTRALIZED AT 0.5%) 0.5 mL/100 mL

Clean All Gel Hand Sanitizer

Warnings

f

or external use only

flammable, keepaway from heat and flame

do not use on open wounds

avoid eyes, ears and mouth. Incase of contact rinse thoroughly with water

Stop and ask doctor if

if irritation occurs

you may report side effects to 1-800-315-4467